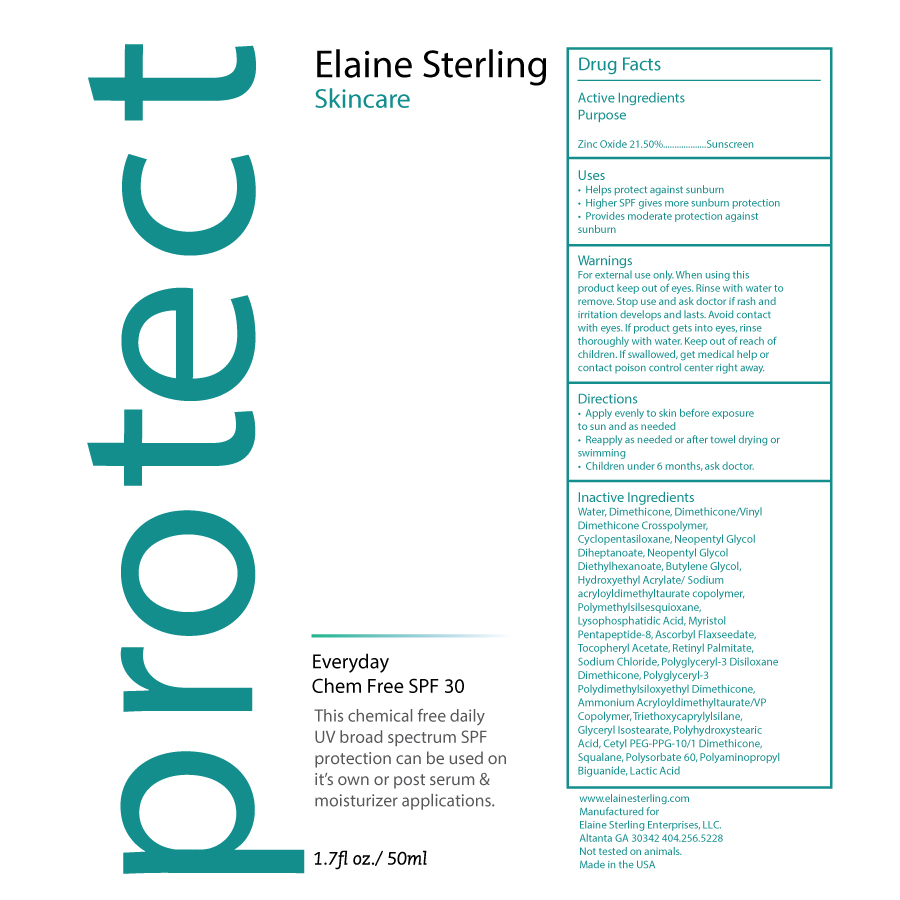 DRUG LABEL: Chem Free SPF 30
NDC: 59958-404 | Form: CREAM
Manufacturer: Owen Biosciences, Inc.
Category: otc | Type: HUMAN OTC DRUG LABEL
Date: 20250113

ACTIVE INGREDIENTS: ZINC OXIDE 21 g/100 g
INACTIVE INGREDIENTS: WATER 35 g/100 g; DIMETHICONE 12 g/100 g; DIMETHICONE/VINYL DIMETHICONE CROSSPOLYMER (SOFT PARTICLE) 8 g/100 g; NEOPENTYL GLYCOL DIHEPTANOATE 2.8 g/100 g; NEOPENTYL GLYCOL DIETHYLHEXANOATE 1.9 g/100 g; BUTYLENE GLYCOL 1.8 g/100 g

-403 Chem Free SPF 30

Active Ingredients Purpose

Zinc Oxide 21.50%...... Sunscreen

Uses

- Helps protect against sunburn
- Higher SPF gives more sunburn protection
- provides moderate protection against sunburn

Warnings

For external use only. When using this product keep out of eyes. Rinse with water to remove. Stop use and ask doctor if rash and irritation develops and lasts. Avoid contact with eyese. If product gets into eyes, rinse thoroughly with water. Keep out of reach of children. If swallowed, get medicl help or contact poison control center right away.

Directions

- Apply evenly to skin before exposure to sun and as needed
- Reapply as needed or after towel drying or swimming
- Children under 6 months, ask doctor.

Dosage & Administration

Apply evenly to skin before exposure and as needed.

Keep out of reach of children

Purpose

Sunscreen